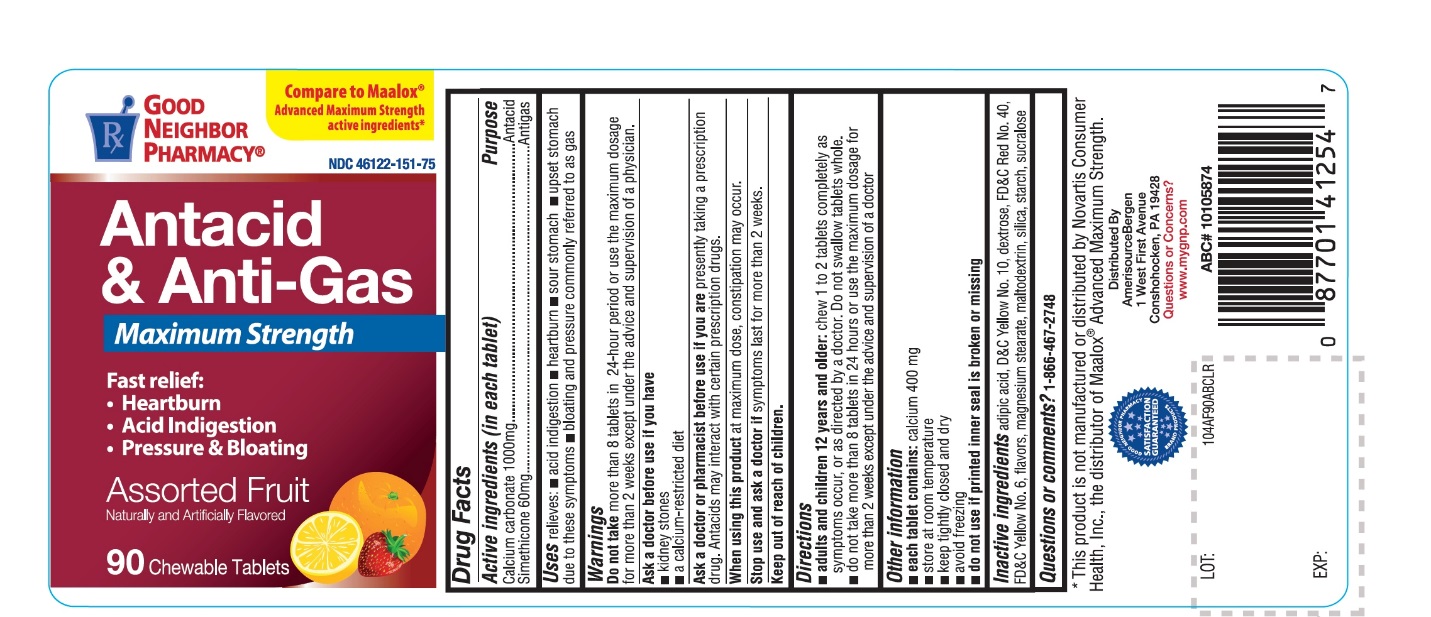 DRUG LABEL: Good Neighbor Pharmacy Antacid and Anti Gas Maximum Strength
NDC: 46122-151 | Form: TABLET, CHEWABLE
Manufacturer: Amerisource Bergen
Category: otc | Type: HUMAN OTC DRUG LABEL
Date: 20250709

ACTIVE INGREDIENTS: CALCIUM CARBONATE 1000 mg/1 1; DIMETHICONE, UNSPECIFIED 60 mg/1 1
INACTIVE INGREDIENTS: ADIPIC ACID; D&C YELLOW NO. 10; DEXTROSE, UNSPECIFIED FORM; FD&C RED NO. 40; FD&C YELLOW NO. 6; MAGNESIUM STEARATE; MALTODEXTRIN; SILICON DIOXIDE; STARCH, CORN; SUCRALOSE

GOOD NEIGHBOR PHARMACY Antacid and Anti-Gas Maximum Strength Assorted Fruit

Active ingredients (in each tablet)

Calcium carbonate 1000 mg

Simethicone 60 mg

Purpose

Antacid

Antigas

Uses

relieves:

- acid indigestion
- heartburn
- sour stomach
- upset stomach due to these symptoms
- bloating and pressure commonly referred to as gas

Warnings

Do not takemore than 8 tablets in 24 hours or use the maximum dosage for more than 2 weeks except under the advice and supervision of a doctor.

Ask a doctor before use if you have

- kidney stones
- a calcium-restricted diet

Ask a doctor or pharmacist before use if you are

presently taking a prescription drug. Antacids may interact with certain prescription drugs.

When using this product

at maximum dose, constipation may occur.

Stop use and ask a doctor if

symptoms persist for more than 2 weeks.

Directions

- adults and children 12 years and older: chew 1 to 2 tablets completely as symptoms occur or as directed by a doctor. Do not swallow tablets whole.
- do not take more than 8 tablets in 24 hours or use the maximum dosage for more than 2 weeks except under the advice and supervision of a doctor

Other information

- e ach tablet contains:calcium 400 mg
- store at room temperature
- Keep tightly closed and dry
- Avoid freezing
- do not use if printed inner seal is broken or missing

Inactive ingredients

adipic acid, dextrose unspecified, flavors, magnesium stearate, maltodextrin, red 40 lake, silica, starch, sucralose, yellow 6 lake, yellow 10 lake

Package/Label Principal Display Panel

NDC: 46122-151-75

Compare to Maalox® Advanced Maximum Strength active ingredients*

GOOD NEIGHBOR PHARMACY®

Antacid & Anti-Gas

Maximum Strength

Fast relief:

- Heartburn
- Acid Indigestion
- Pressure & Bloating
- Assorted Fruit
- Naturally and Artificially Flavored

90 Chewable Tablets

Distributed By

Amerisource Bergen

1 West First Avenue

Conshohocken, PA 19428

Visit us at www.mygnp.com

*This product is not manufactured or distributed by Novartis Consumer Health, Inc., the distributor of Maalox® Advanced Maximum Strength.

SATISFACTION GUARANTEED

ABC# 10105874